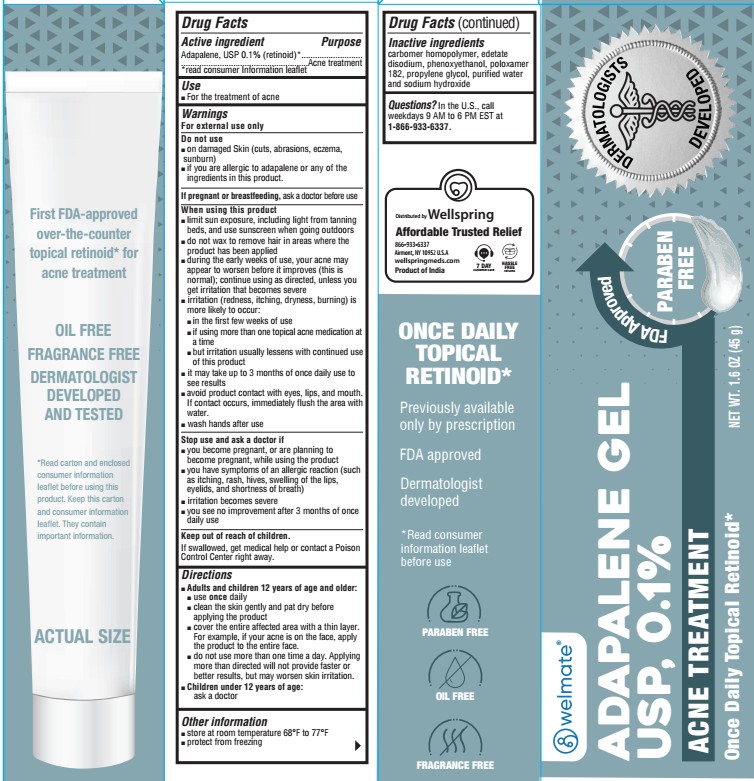 DRUG LABEL: Adapalene
NDC: 73581-216 | Form: GEL
Manufacturer: YYBA Corp
Category: otc | Type: HUMAN OTC DRUG LABEL
Date: 20260203

ACTIVE INGREDIENTS: ADAPALENE 1 mg/1 g
INACTIVE INGREDIENTS: PROPYLENE GLYCOL; WATER; CARBOMER HOMOPOLYMER TYPE C; EDETATE DISODIUM; PHENOXYETHANOL; POLOXAMER 182; SODIUM HYDROXIDE

GLEN MARK ADAPALENE 73581-216

Active ingredient

Adapalene USP 0.1% (retinoid)*
*read consumer information leaflet

Purpose

Acne treatment

Use

For the treatment of acne

Warnings

For external use only

Do not use

- on damaged skin (cuts, abrasions eczema, sunburn)
- if you are allergic to adapalene or any of the ingredients in this product

Pregnancy/Breastfeeding

ask a doctor before use.

When using this product

- limit sun exposure, including light from tanning beds, and use sunscreen when going outdoors.
- do not wax to remove hair in areas where the product has been applied
- during the early weeks of use, your acne may appear to worsen before it improves (this is normal); continue using as directed, unless you get irritation that become severe
- irritation (redness, itching, dryness, burning) is more likely to occur:
- in the first few weeks of use
- if using more than one topical acne medication at a time
- but irritation usually lessens with continued use of this product
- it may take up to 3 months of once daily use to see result
- avoid product contact eyes, lips, and month. If contact occurs immediately flush the area with water.
- wash hands after use

Stop use and ask a doctor if

- you become pregnant, or planning to become pregnant while using this product
- you have symptoms of an allergic reaction (such as itching, rash, hives, swelling of the lips, eyelids, and shortness of breath)
- irritation become severe
- you see no improvement after 3 months of once daily use

Keep out of reach of children.

If swallowed, get medical help or contact a Poison Control Center (1-800-222-1222) right away.

Directions

- Adults and children 12 years of age and older:
- use once daily
- clean the skin gently and pat dry before applying the product
- cover the entire affected area with a thin layer. For example, if your acne in on the face, apply the product to the entire face.
- do not use more than one time a day. Applying more than directed will not provide faster or better results, but may worsen skin irritation.
- Children under 12 years of age: ask a doctor

Other information

- store at rooms temperature 68º to 77ºF
- protect from freezing

Inactive ingredients

carbomer homopolymer typeC, edetate disodium, methylparabem, poloxamer 182, propylene glycol, purified water. May contain hydrochloric acid and/or sodium hydroxide to adjust pH.

Questions or comments?

Call 1-877-753-3935

Monday-Friday 9AM-5PM EST

Principal Display Panel

†Compare to the active ingredient in Differin® Gel
Adapalene Gel USP 0.1%
Acne Treatment
Previously available only by prescription
Once daily topical retinoid*
Oil free
Fragrance free
Dermatologist developed and tested
NET WT OZ (g)

*READ CONSUMER INFORMATION LEAFLET BEFORE USE
*Read cartonand enclosed consumer information leaflet before using this product. Keep this carton and consumer information leaflet. They contain important information.
†This product is not manufactured or distributed by Galderma Laboratories, L.P. distributor of Differin® Gel.
DISTRIBUTED BY
Wellspring Meds.

NDC 73581-216-45

Adapalene Gel USP, 0.1%

NET WT. 1.6 OZ (45 g)